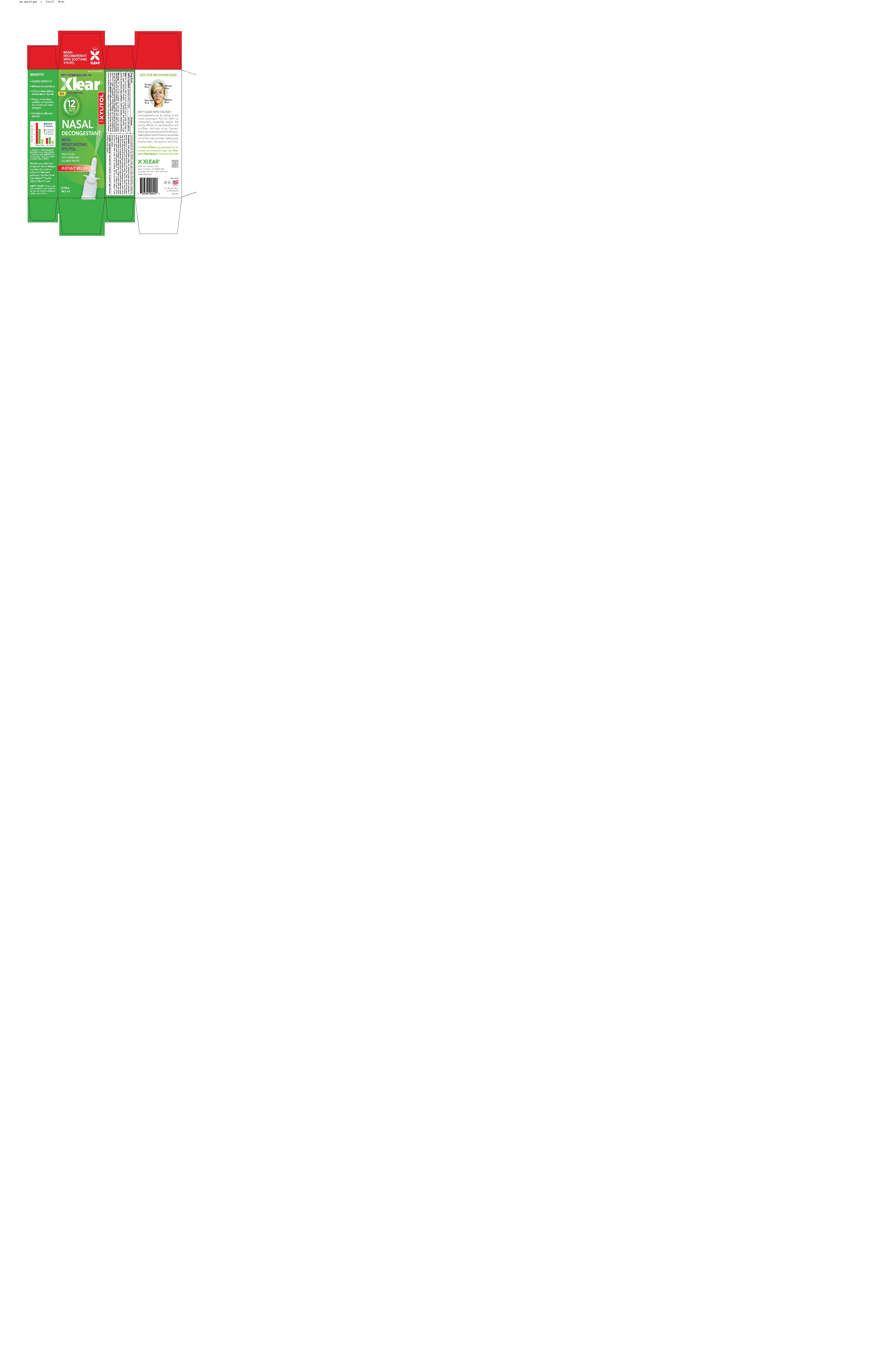 DRUG LABEL: Xlear Nasal Decongestant
NDC: 27017-018 | Form: LIQUID
Manufacturer: Xlear Inc.
Category: otc | Type: HUMAN OTC DRUG LABEL
Date: 20251106

ACTIVE INGREDIENTS: OXYMETAZOLINE HYDROCHLORIDE 0.0005 g/1 g
INACTIVE INGREDIENTS: WATER; CITRUS PARADISI (GRAPEFRUIT) SEED OIL; XYLITOL; BENZALKONIUM CHLORIDE

Warnings

The use of this container by more than one person may spread infection. Keep out of reach of children. Clean nozzle after each use & replace the cap. Do not exceed recommended dosage. Do not use this product for more than 3 days. If pregnant or breast-feeding, ask a health professional before use. Ask a physician before use if you have - heart disease - high blood pressure - thyroid disease - diabetes - trouble urinating due to enlarged prostate gland - Not for children under age 6 unless directed by a physician.

Uses

Uses: For temporary relief of nasal decongestion due to colds, hay fever or upper respiratory allergies, or associated with sinusitis. Helps soothe & moisturize nasal passages. Thins & loosens mucous secretions.

Directions

Directions: Shake well before using. The metered pump sprayer provides a precise amount of soothing spray in a fine mist. Clear the nasal passage-way by gently blowing your nose before using. Prior to initial use, remove cap, prime the pump by holding it upright and pumping one or more times until the solution is dispensed. Insert nozzle into nostril and depress pump completly while breathing in through nose. Clean nozzle after use. Ages 6 years to adult (with adult supervision) - spray 1-2 times in each nostril not more often than every 10 to 12 hours. Do not exceed 2 doses in any 24-hour period.

Warnings

Keep out of reach of children

WARNINGS

The use of this container by more than one person may spread infection. Keep out of reach of children. Clean nozzle after each use & replace the cap. Do not exceed recommended dosage. Do not use this product for more than 3 days. If pregnant or breast-feeding, ask a health professional before use. Ask a physician before use if you have - heart disease - high blood pressure - thyroid disease - diabetes - trouble urinating due to enlarged prostate gland - Not for children under age 6 unless directed by a physician.

active section

Active ingredients: Oxymetazoline HCL 0.05% ................. Nasal Decongestant

directions

Directions: Shake well before using. The metered pump sprayer provides a precise amount of soothing spray in a fine mist. Clear the nasal passage-way by gently blowing your nose before using. Prior to initial use, remove cap, prime the pump by holding it upright and pumping one or more times until the solution is dispensed. Insert nozzle into nostril and depress pump completely while breathing in through nose. Clean nozzle after use. Ages 6 years to adult (with adult supervision) - spray 1-2 times in each nostril not more often than every 10 to 12 hours. Do not exceed 2 doses in any 24-hour period.

inactives

Inactive ingredients: Benzalkonium Chloride, Grapefruit Seed Extract, Purified Water, Xylitol

OTC Purpose

Uses: For temporary relief of nasal decongestion due to colds, hay fever or upper respiratory allergies, or associated with sinusitis. Helps soothe & moisturize nasal passages. Thins & loosens mucous secretions.